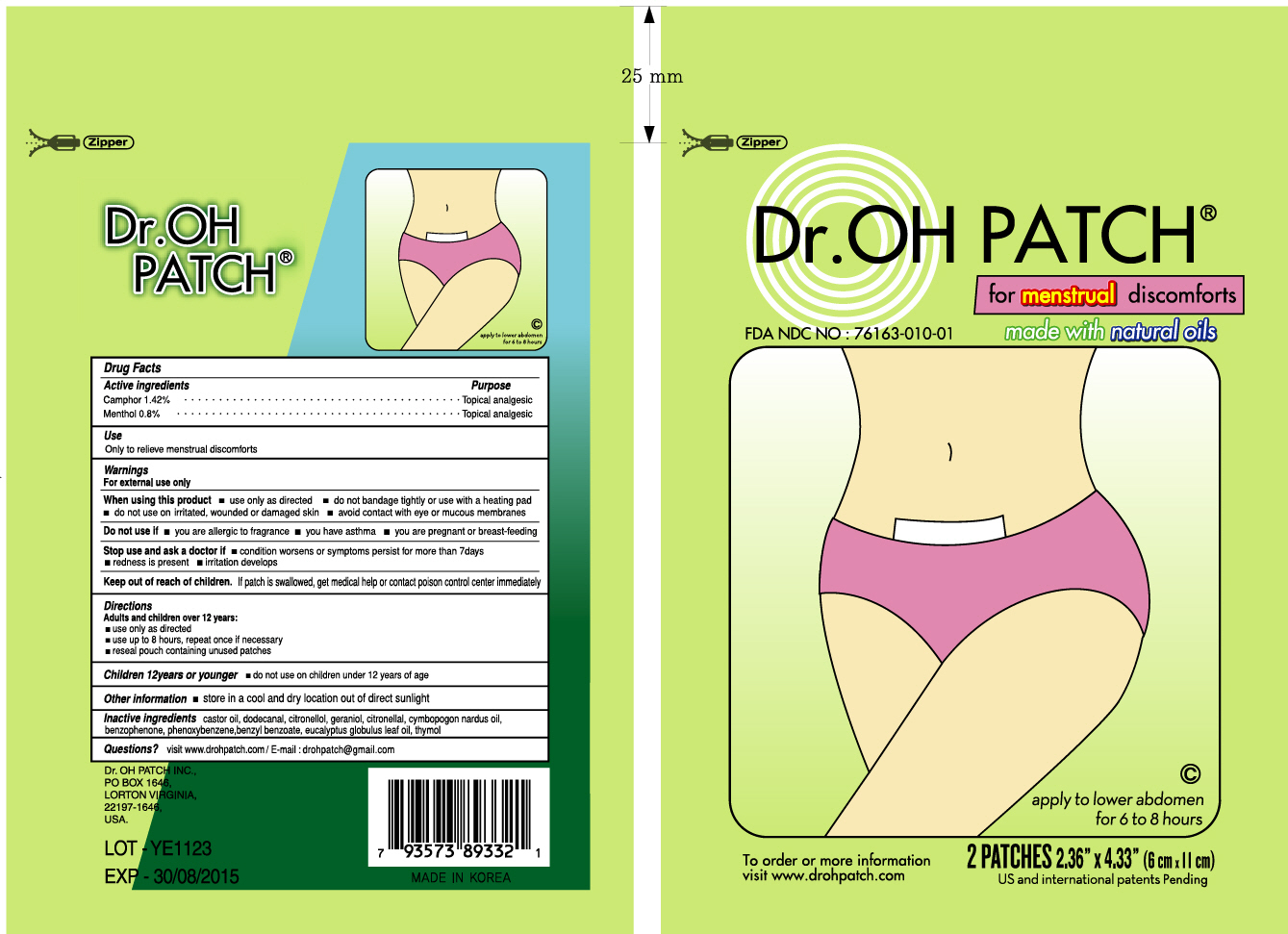 DRUG LABEL: DR.OH PATCH
NDC: 76163-010 | Form: PATCH
Manufacturer: YEPHARM
Category: otc | Type: HUMAN OTC DRUG LABEL
Date: 20110825

ACTIVE INGREDIENTS: CAMPHOR (NATURAL) 28.4 mg/2000 mg; MENTHOL 16 mg/2000 mg
INACTIVE INGREDIENTS: EUCALYPTUS GLOBULUS LEAF; THYMOL; CASTOR OIL; .BETA.-CITRONELLOL, (R)-; GERANIOL; CITRONELLAL; CITRONELLA OIL; BENZOPHENONE; BENZYL BENZOATE; ETHYL ACETATE

Drug Facts

ACTIVE INGREDIENT

Active ingredients: CAMPHOR (NATURAL) 1.42%, MENTHOL 0.8%

Inactive ingredients:

Eucalyptus globulus leaf oil, Thymol, castor oil, dodecanal, citronellol, geraniol, citronellal, cymbopogon nardus oil, benzophenone, phenoxybenzene, benzyl benzoate

Purpose:

Topical analgesic

Warnings:

For external use only.

When using this product
- use only as directed.
- do not bandage tightly or use with a heating pad.
- do not use on irritated, wounded or damaged skin.
- avoid contact with eye or mucous membranes.

Do not use if
- you are allergic to fragrance.
- you have asthma.
- you are pregnant or breast-feeding.

Stop use if
- condition worsens or symptoms persist for more than 7days.
- redness is present.
- irritation develops.

Ask a doctor if
- condition worsens or symptoms persist for more than 7days.
- redness is present.
- irritation develops.

Keep out of reach of children:

If patch is swallowed, get medical help or contact poison control center immediately.

Indication and usage:

Adults and children over 12 years
- use only as directed.
- do not use on children under 12 years of age.
- use up to 8 hours, repeat once if necessary.
- reseal pouch containing unused patches.

Storage:

Store in a cool and dry location out of direct sunlight.

Questions:

Phone: 608-362-6915
E-mail: drohpatch@gmail.com

Dosage and administration:

Use up to 8 hours, repeat once if necessary.